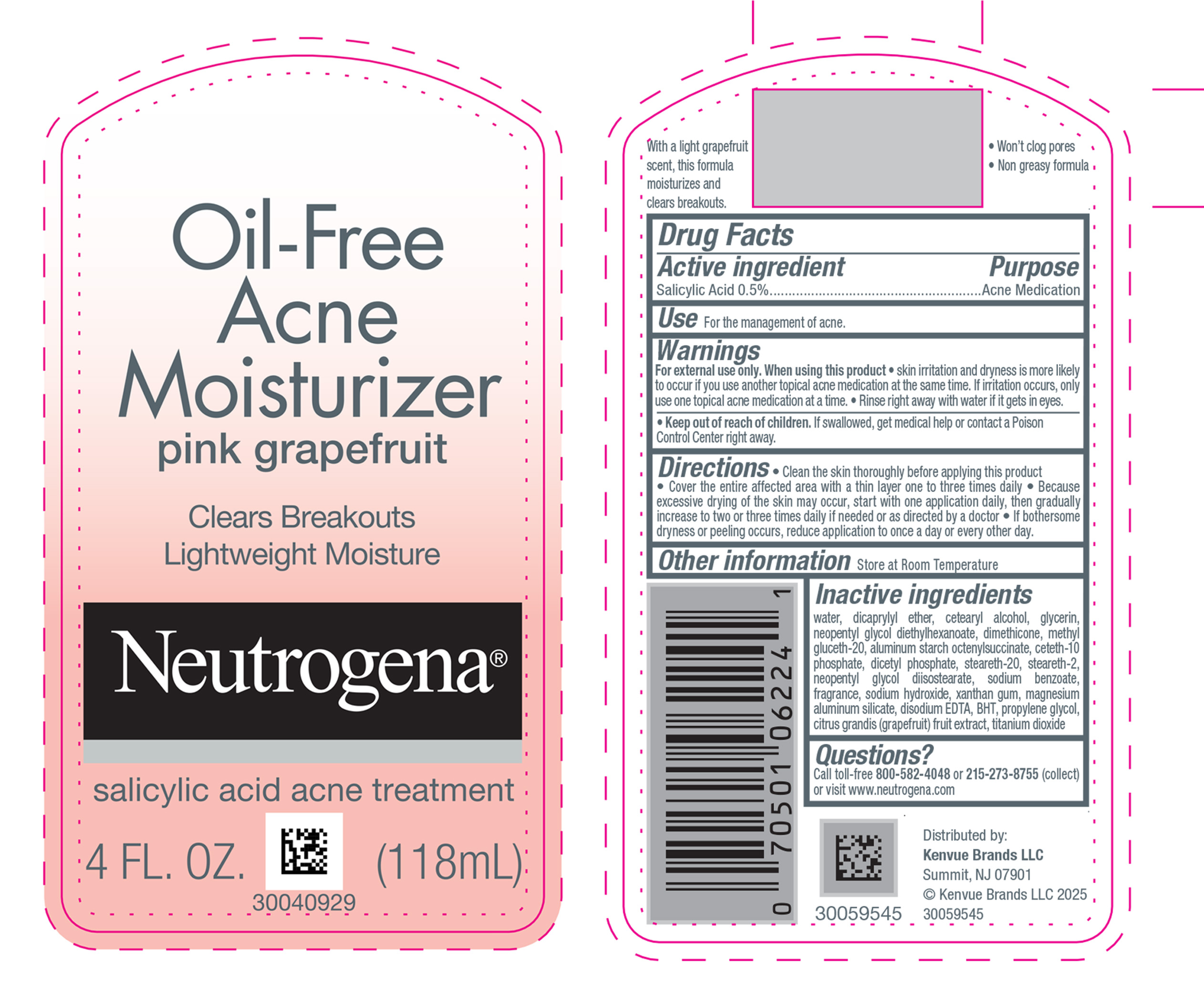 DRUG LABEL: Neutrogena Oil Free Acne Moisturizer Pink Grapefruit
NDC: 69968-0193 | Form: LOTION
Manufacturer: Kenvue Brands LLC
Category: otc | Type: HUMAN OTC DRUG LABEL
Date: 20250305

ACTIVE INGREDIENTS: SALICYLIC ACID 5 mg/1 mL
INACTIVE INGREDIENTS: WATER; DICAPRYLYL ETHER; CETOSTEARYL ALCOHOL; GLYCERIN; NEOPENTYL GLYCOL DIETHYLHEXANOATE; DIMETHICONE; METHYL GLUCETH-20; ALUMINUM STARCH OCTENYLSUCCINATE; CETETH-10 PHOSPHATE; DIHEXADECYL PHOSPHATE; STEARETH-20; STEARETH-2; NEOPENTYL GLYCOL DIISOSTEARATE; SODIUM BENZOATE; SODIUM HYDROXIDE; EDETATE DISODIUM; XANTHAN GUM; MAGNESIUM ALUMINUM SILICATE; BUTYLATED HYDROXYTOLUENE; PROPYLENE GLYCOL; PUMMELO; TITANIUM DIOXIDE

Neutrogena ® Oil-Free Acne Moisturizer pink grapefruit

Drug Facts

Active ingredient

Salicylic Acid 0.5%

Purpose

Acne Medication

Use

For the management of acne.

Warnings

For external use only.

When using this product

- skin irritation and dryness is more likely to occur if you use another topical acne medication at the same time. If irritation occurs, only use one topical acne medication at a time.
- Rinse right away with water if it gets in eyes.

- Keep out of reach of children. If swallowed, get medical help or contact a Poison Control Center right away.

Directions

- Clean the skin thoroughly before applying this product
- Cover the entire affected area with a thin layer one to three times daily
- Because excessive drying of the skin may occur, start with one application daily, then gradually increase to two or three times daily if needed or as directed by a doctor
- If bothersome dryness or peeling occurs, reduce application to once a day or every other day.

Other information

Store at Room Temperature

Inactive ingredients

water, dicaprylyl ether, cetearyl alcohol, glycerin, neopentyl glycol diethylhexanoate, dimethicone, methyl gluceth-20, aluminum starch octenylsuccinate, ceteth-10 phosphate, dicetyl phosphate, steareth-20, steareth-2, neopentyl glycol diisostearate, sodium benzoate, fragrance, sodium hydroxide, xanthan gum, magnesium aluminum silicate, disodium EDTA, BHT, propylene glycol, citrus grandis (grapefruit) fruit extract, titanium dioxide

Questions?

Call toll-free 800-582-4048 or 215-273-8755 (collect) or visit www.neutrogena.com

Distributed By:

Kenvue Brands LLC
Summit, NJ 07901

PRINCIPAL DISPLAY PANEL - 118 mL Bottle Label

Oil-Free
Acne
Moisturizer
pink grapefruit

Clears Breakouts
Lightweight Moisture

Neutrogena®

salicylic acid acne treatment

4 FL. OZ. (118mL)